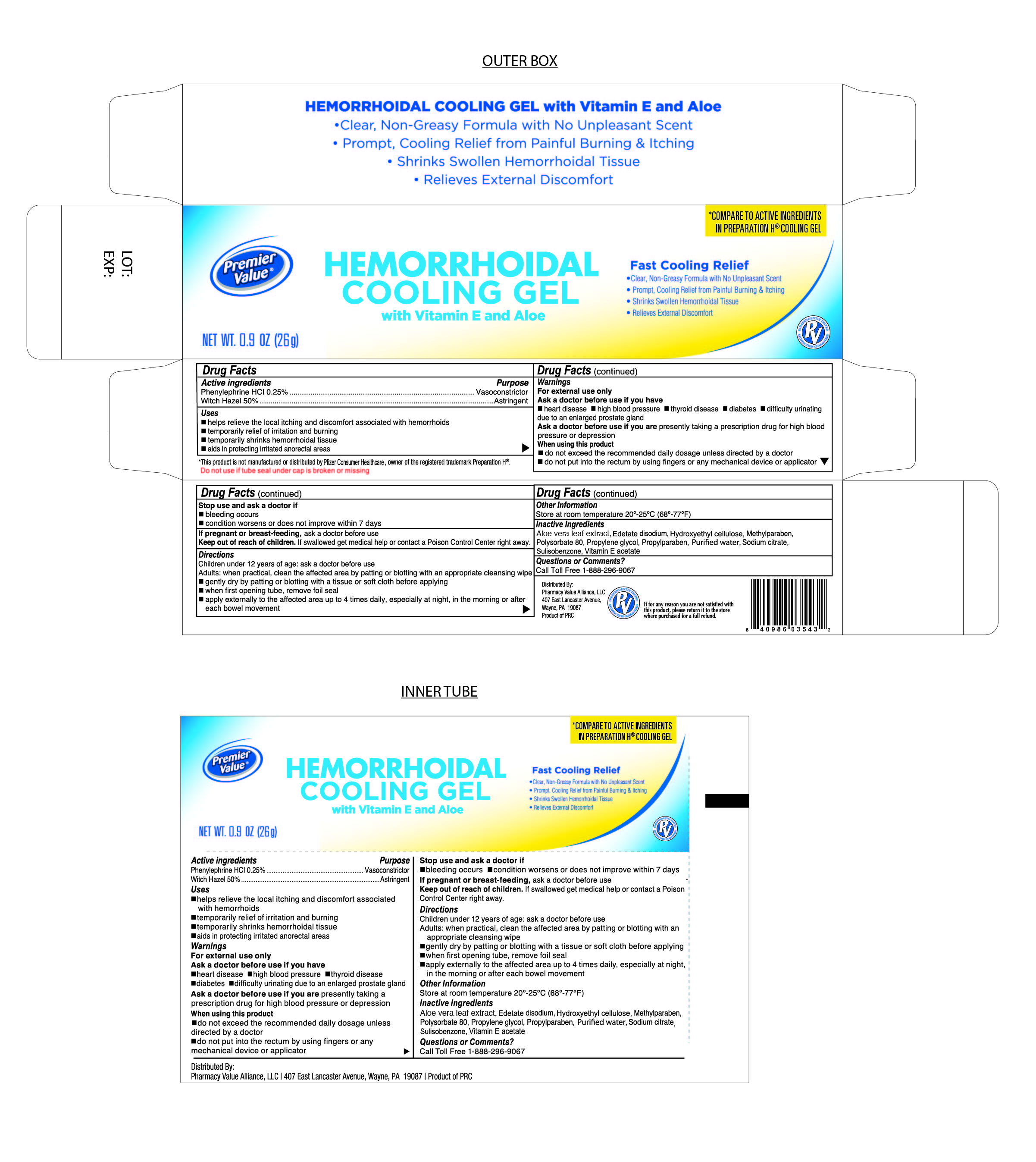 DRUG LABEL: Hemorroidal Cooling gel
NDC: 68016-054 | Form: GEL
Manufacturer: Pharmacy Value Alliance, LLC
Category: otc | Type: HUMAN OTC DRUG LABEL
Date: 20241220

ACTIVE INGREDIENTS: WITCH HAZEL 0.5 g/100 g; PHENYLEPHRINE HYDROCHLORIDE 0.25 g/100 g
INACTIVE INGREDIENTS: POLYSORBATE 80; METHYLPARABEN; SULISOBENZONE; EDETATE DISODIUM; ALOE VERA LEAF; WATER; SODIUM CITRATE; PROPYLENE GLYCOL; .ALPHA.-TOCOPHEROL ACETATE, D-; PROPYLPARABEN; HYDROXYETHYL CELLULOSE (2000 CPS AT 1%)

Hemorrhoidal Cooling Gel

Active Ingredient

Phenylephrine HCI 0.25%

Purpose

Vasoconstrictor

Active Ingredient

Witch Hazel 50%

Purpose

Astringent

Uses

- Helps relieve the local itching and discomfort associated with hemorrhoids
- temporarily relief of irritation and burning
- temporarily shrinks hemorrhoidal tissue
- aids in protecting irritated anorectal areas

Stop use and ask a doctor

- bleeding occurs
- condition worsens or does not improve within 7 days

If pregnant or breast feeding

Ask a doctor before use

Keep out of the reach of children

If swallowed get medical help or contact Poison Control Center right away

Directions

Children under 12 years of age; ask a doctor before use

Adults: when practical, clean the affected area by patting or blotting with an appropriate cleansing wipe

- gently dry by patting or blotting with a tissue or soft cloth before applying
- when first opening tube, remove foil seal
- apply externally to the affected area up to 4 times daily, especially at night, in the morning or after each bowel movement

Warnings

For External Use Only

Ask doctor before use if you have

- heart disease
- high blood pressure
- thyroid disease
- diabetes
- difficulty urinating due to an enlarged prostate gland

Ask doctor before use if you are presently taking a prescription drug for high blood pressure or depression.

When using this product

- do not exceed the recommended daily dosage unless directed by a doctor
- do not put into the rectum by using fingers or any mechanical device or applicator

Other information

Store at room temperature 20°-25°C (68°-77°F)

Do not use if tube seal under cap is broken or missing

** This product is not manufactured or distributed by Wyeth Consumer Healthcare Inc. owner of the registered trademark Preparation H®

Inactive Ingredients

Aloe barbadensis gel, benzophenone-4, Acetate disodium, Hydroxyethylcellulose, methylparaben, polysorbate 80, propylene glycol, propylparaben, sodium citrate, Vitamin E, water

Questions or Comments

Call Toll Free 1-888-296-9067

Distributed By

Premier Value Alliance, LLC.

407 East Lancaster Avenue

Wayne, PA. 19087 USA

Product of PRC

Packaging

Hemorrhoidal Cooling Gel